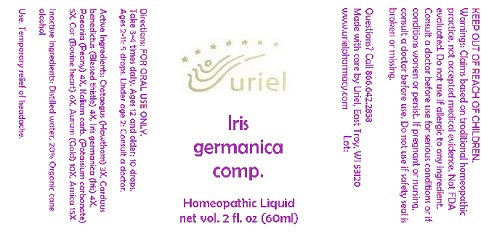 DRUG LABEL: Iris germanica comp.
NDC: 48951-5072 | Form: LIQUID
Manufacturer: Uriel Pharmacy Inc.
Category: homeopathic | Type: HUMAN OTC DRUG LABEL
Date: 20180426

ACTIVE INGREDIENTS: HAWTHORN LEAF WITH FLOWER 3 [hp_X]/1 mL; CENTAUREA BENEDICTA 4 [hp_X]/1 mL; C12-17 ALKANE 4 [hp_X]/1 mL; PAEONIA OFFICINALIS ROOT 4 [hp_X]/1 mL; POTASSIUM CARBONATE 5 [hp_X]/1 mL; BEEF HEART 6 [hp_X]/1 mL; GOLD 10 [hp_X]/1 mL; ARNICA MONTANA 15 [hp_X]/1 mL
INACTIVE INGREDIENTS: WATER; ALCOHOL

Iris germanica comp.

INDICATIONS AND USAGE

Directions: FOR ORAL USE ONLY.

DOSAGE AND ADMINISTRATION

Take 3-4 times daily. Ages 12 and older: 10 drops. Ages 2-11: 5 drops. Under age 2: Consult a doctor.

ACTIVE INGREDIENT

Active Ingredients: Crataegus (Hawthorn) 3X, Carduus benedictus (Blessed thistle) 4X, Iris germanica (Iris) 4X, Paeonia (Peony) 4X, Kalium carb. (Potassium carbonate) 5X, Cor (Bovine heart) 6X, Aurum (Gold) 10X, Arnica 15X

Inactive Ingredients: Distilled water, Organic cane alcohol

PURPOSE

Use: Temporary relief of headache.

KEEP OUT OF REACH OF CHILDREN.

WARNINGS

Warnings: Claims based on traditional homeopathic practice, not accepted medical evidence. Not FDA evaluated. Do not use if allergic to any ingredient. Consult a doctor before use for serious conditions or if conditions worsen or persist. If pregnant or nursing, consult a doctor before use. Do not use if safety seal is broken or missing.

QUESTIONS

Questions? Call 866.642.2858 Made with care by Uriel, East Troy, WI 53120 www.urielpharmacy.com